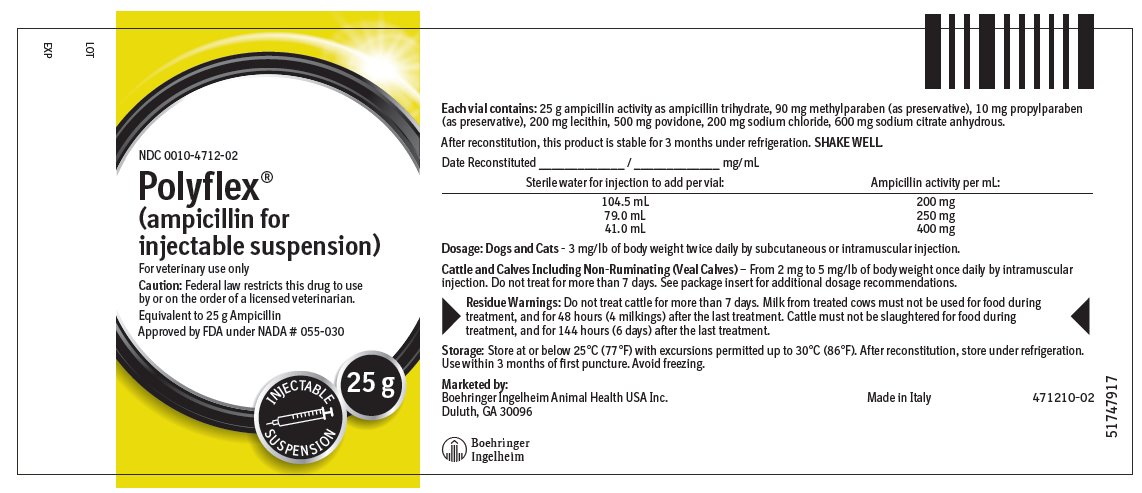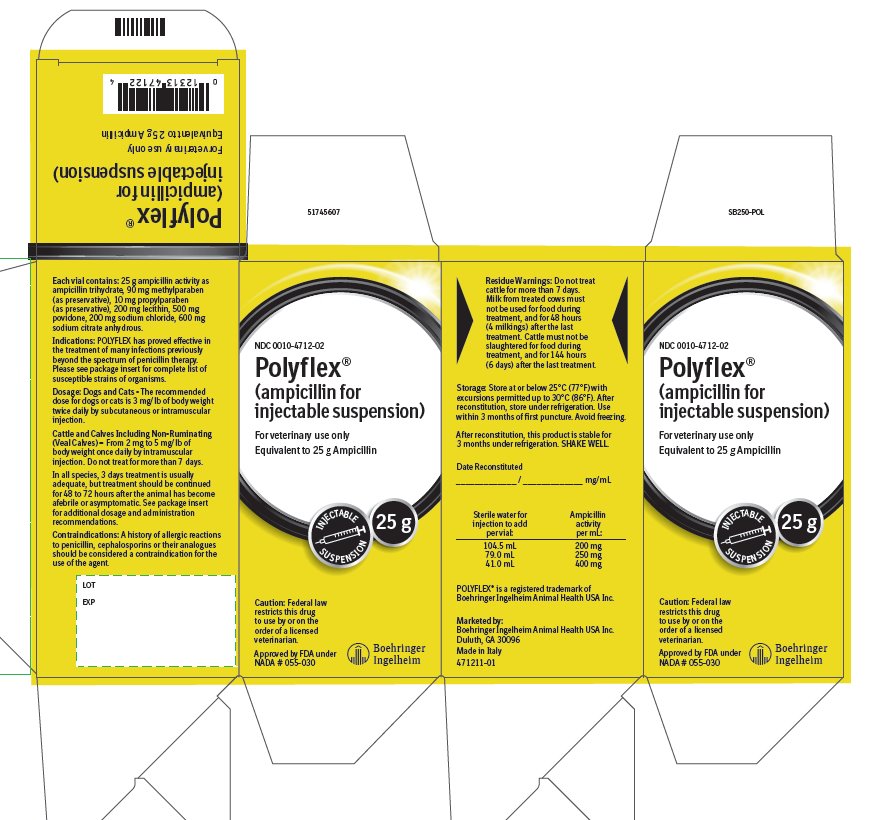 DRUG LABEL: POLYFLEX
NDC: 0010-4712 | Form: INJECTION, POWDER, FOR SUSPENSION
Manufacturer: Boehringer Ingelheim Animal Health USA Inc.
Category: animal | Type: PRESCRIPTION ANIMAL DRUG LABEL
Date: 20240917

ACTIVE INGREDIENTS: AMPICILLIN TRIHYDRATE 250 mg/1 mL
INACTIVE INGREDIENTS: METHYLPARABEN 0.9 mg/1 mL; PROPYLPARABEN 0.1 mg/1 mL; LECITHIN, SOYBEAN 2 mg/1 mL; POVIDONE K30 5 mg/1 mL; SODIUM CHLORIDE 2 mg/1 mL; ANHYDROUS TRISODIUM CITRATE 6 mg/1 mL

Polyflex®
(ampicillin for injectable suspension)

For veterinary use only

CAUTION:

Federal law restricts this drug to use by or on the order of a licensed veterinarian.

DESCRIPTION:

POLYFLEX (ampicillin for injectable suspension) is a broad-spectrum penicillin which has bactericidal activity against a wide range of common gram-positive and gram-negative bacteria.

Each 25 g vial contains: 25 g ampicillin activity as ampicillin trihydrate, 90 mg methylparaben (as preservative), 10 mg propylparaben (as preservative), 200 mg lecithin, 500 mg povidone, 200 mg sodium chloride, 600 mg sodium citrate anhydrous.

INDICATIONS:

POLYFLEX has proved effective in the treatment of many infections previously beyond the spectrum of penicillin therapy. This drug is particularly indicated in the treatment of the following infections caused by susceptible strains of organisms:

Dogs and Cats — Respiratory Tract Infections: Upper respiratory infections, tonsillitis and bronchopneumonia due to hemolytic streptococci, Staphylococcus aureus, Escherichia coli,

Proteus mirabilis and Pasteurella spp.

Urinary Tract Infections due to Proteus mirabilis, Escherichia coli, Staphylococcus spp., hemolytic streptococci and Enterococcus spp.

Gastrointestinal Infections due to Enterococcus spp., Staphylococcus spp. and Escherichia coli.

Skin, Soft Tissue and Post-Surgical Infections: Abscesses, pustular dermatitis, cellulitis and infections of the anal gland, due to Escherichia coli, Proteus mirabilis, hemolytic streptococci, Staphylococcus spp. and Pasteurella spp.

Cattle and Calves Including Non-Ruminating (Veal Calves) — Respiratory Tract Infections:

Bacterial pneumonia (shipping fever, calf pneumonia and bovine pneumonia) caused by Aerobacter spp., Klebsiella spp., Staphylococcus spp., Streptococcus spp., Pasteurella multocida and E. coli susceptible to ampicillin trihydrate.

DOSAGE:

The dosage of POLYFLEX will vary according to the animal being treated, the severity of the infection and the animal’s response.

Dogs and Cats — The recommended dose for dogs or cats is 3 mg/lb of body weight administered twice daily by subcutaneous or intramuscular injection.

Cattle and Calves Including Non-Ruminating (Veal Calves) — From 2 mg to 5 mg/lb of body weight once daily by intramuscular injection. Do not treat for more than 7 days.

In all species, 3 days treatment is usually adequate, but treatment should be continued for 48 to 72 hours after the animal has become afebrile or asymptomatic.

DIRECTIONS FOR USE:

The multi-dose dry-filled vials should be reconstituted to the desired concentration by adding the required amount of Sterile Water for Injection, USP, according to label directions. SHAKE WELL.

The appearance will be white to pale yellow in color.

At the time of reconstitution the vial should be dated and the concentration noted on the label.

CONTRAINDICATIONS:

A history of allergic reactions to penicillin, cephalosporins or their analogues should be considered a contraindication for the use of this agent.

RESIDUE WARNINGS:

Do not treat cattle for more than 7 days. Milk from treated cows must not be used for food during treatment, and for 48 hours (4 milkings) after the last treatment. Cattle must not be slaughtered for food during treatment, and for 144 hours (6 days) after the last treatment.

PRECAUTIONS:

Because it is a derivative of 6-aminopenicillanic acid, POLYFLEX has the potential for producing allergic reactions. If they should occur, POLYFLEX should be discontinued and the subject treated with the usual agents (antihistamines, pressor amines, corticosteroids).

CLINICAL PHARMACOLOGY:

The antimicrobial action of ampicillin is bactericidal, and only a small percentage of the antibiotic is serum-bound. Peak serum levels in dogs and cats are reached approximately one-half hour following subcutaneous or intramuscular injection, and in cattle 1 hour to 2 hours following intramuscular injection.

In vitro studies have demonstrated sensitivity of the following organisms to ampicillin: gram-positive bacteria – alpha- and beta-hemolytic streptococci, staphylococci (non-penicillinase-producing), Bacillus anthracis and most strains of enterococci and clostridia; gram-negative bacteria – Proteus mirabilis, E. coli and many strains of Salmonella and Pasteurella multocida.

The drug does not resist destruction by penicillinase and, hence, is not effective against strains of staphylococci resistant to penicillin G. Susceptibility tests should be conducted to estimate the in vitro susceptibility of bacterial isolates to ampicillin.

STORAGE:

Store at or below 25°C (77°F) with excursions permitted up to 30°C (86°F). After reconstitution, store under refrigeration. Use within 3 months of first puncture. Avoid freezing.

HOW SUPPLIED:

POLYFLEX (ampicillin for injectable suspension) is supplied in vials containing 25 g ampicillin activity as ampicillin trihydrate.

NDC 0010-4712-02 — 25 g per vial

POLYFLEX® is a registered trademark of Boehringer Ingelheim Animal Health USA Inc.

© 2020 Boehringer Ingelheim Animal Health USA Inc. All rights reserved.

Approved by FDA under NADA # 055-030

Marketed by:

Boehringer Ingelheim Animal Health USA Inc.

Duluth, GA 30096

Made in Italy

Rev. 9/2020
471209-01

Principal Display Panel – 25 g Vial Label

NDC 0010-4712-02

Polyflex®

(ampicillin for injectable suspension)

For veterinary use only

Caution: Federal law restricts this drug to use by or on the order of a licensed veterinarian.

Equivalent to 25 g Ampicillin

Approved by FDA under NADA # 055-030

Principal Display Panel - 25 g Display Carton

NDC 0010-4712-02

Polyflex®

(ampicillin for injectable suspension)

For veterinary use only

Caution: Federal law restricts this drug to use by or on the order of a licensed veterinarian.

Equivalent to 25 g Ampicillin

Approved by FDA under NADA # 055-030